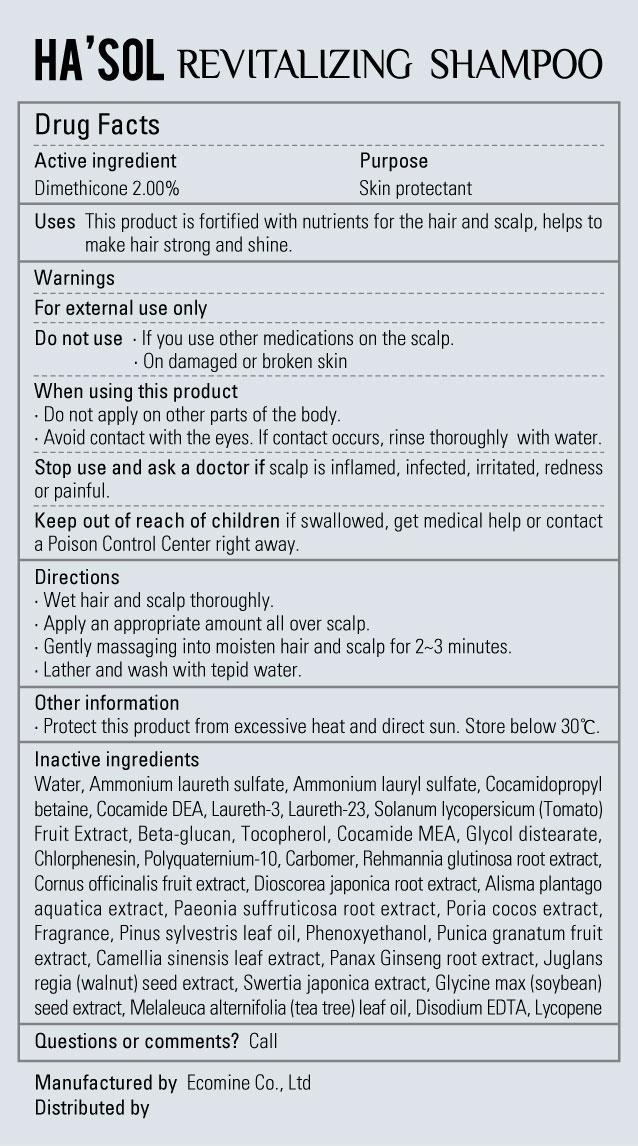 DRUG LABEL: Hasol Revitalizing
NDC: 51270-114 | Form: GEL
Manufacturer: Ecomine Co Ltd
Category: otc | Type: HUMAN OTC DRUG LABEL
Date: 20130701

ACTIVE INGREDIENTS: DIMETHICONE 2 g/300 g
INACTIVE INGREDIENTS: WATER; AMMONIUM LAURYL SULFATE; COCAMIDOPROPYL BETAINE; COCO DIETHANOLAMIDE; LAURETH-3; LAURETH-23; TOMATO; TOCOPHEROL; COCO MONOETHANOLAMIDE; GLYCOL DISTEARATE; CHLORPHENESIN; POLYQUATERNIUM-10 (30000 MPA.S AT 2%); REHMANNIA GLUTINOSA ROOT; CORNUS OFFICINALIS FRUIT; DIOSCOREA JAPONICA TUBER; ALISMA PLANTAGO-AQUATICA TOP; PAEONIA SUFFRUTICOSA ROOT; FU LING; PINE NEEDLE OIL (PINUS SYLVESTRIS); PHENOXYETHANOL; POMEGRANATE; GREEN TEA LEAF; ASIAN GINSENG; ENGLISH WALNUT; SWERTIA JAPONICA; SOYBEAN; TEA TREE OIL; EDETATE DISODIUM; LYCOPENE

Hasol Revitalizing Shampoo

Drug Facts

Active Ingredient

Dimethicone 2.00%

Purpose

Skin protectant

Keep out of Reach of Children

Stop use and ask a doctor if scalp is inflamed, infected, irritated, redness or painful.

Keep out of reach of children if swallowed, get medical help or contact a Poison Control Center right away.

Indication & Usage

Directions
■ Wet hair and scalp thoroughly
■ Apply an appropriate amount all over scalp
■ Gently massaging into moisten hair and scalp for 2~3 minutes
■ Lather and wash with tepid water

Warnings

For external use only

Do not use ■ If you use other medications on the scalp.
■ On damaged or broken skin

When using this product
■ Do not apply on other parts of the body
■ Avoid contact with the eyes. If contact occurs, rinse thoroughly with water.

Dosage & Administration

Uses
■ This product is fortified with nutrients for the hair and scalp, helps to make hair strong and shine.

Inactive ingredient

Water, Ammonium laureth sulfate, Ammonium lauryl sulfate, Cocamidopropyl betaine, Cocamide DEA, Laureth-3, Laureth-23, Solanum lycopersicum (Tomato) Fruit Extract, Beta-glucan, Tocopherol, Cocamide MEA, Glycol distearate, Chlorphenesin, Polyquaternium-10, Carbomer, Rehmannia glutinosa root extract, Cornus officinalis fruit extract, Dioscorea japonica root extract, Alisma plantago aquatica extract, Paeonia suffruticosa root extract, Poria cocos extract, Fragrance, Pinus sylvestris leaf oil, Phenoxyethanol, Punica granatum fruit extract, Camellia sinensis leaf extract, Panax Ginseng root extract, Juglans regia (walnut) seed extract, Swertia japonica extract, Glycine max (soybean) seed extract, Melaleuca alternifolia (tea tree) leaf oil, Disodium EDTA, Lycopene

Hasol Revitalizing Shampoo

Net WT. 10.14 FL OZ(500ml)